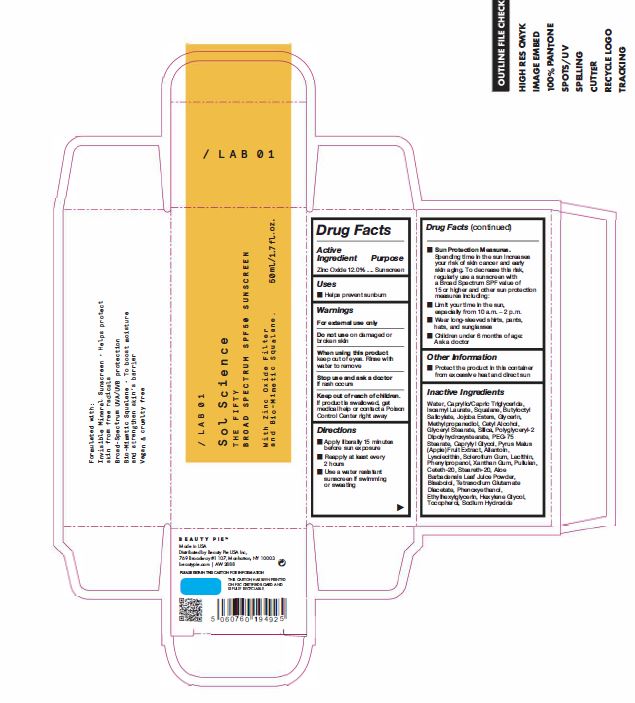 DRUG LABEL: SOL Science The Fifty
NDC: 83282-139 | Form: LOTION
Manufacturer: Beauty Pie
Category: otc | Type: HUMAN OTC DRUG LABEL
Date: 20251113

ACTIVE INGREDIENTS: ZINC OXIDE 132 mg/1 mL
INACTIVE INGREDIENTS: LECITHIN, SOYBEAN; POLYGLYCERYL-2 DIPOLYHYDROXYSTEARATE; PHENYLPROPANOL; HYDROLYZED JOJOBA ESTERS (ACID FORM); METHYLPROPANEDIOL; CAPRYLYL GLYCOL; XANTHAN GUM; ISOAMYL LAURATE; HEXYLENE GLYCOL; TOCOPHEROL; CETYL ALCOHOL; ETHYLHEXYLGLYCERIN; GLYCERIN; SILICON DIOXIDE; WATER; .ALPHA.-BISABOLOL, (+)-; BUTYLOCTYL SALICYLATE; CETETH-20; PULLULAN; SQUALANE; STEARETH-20; CYCLODEXTRINS

SOL Science The Fifty